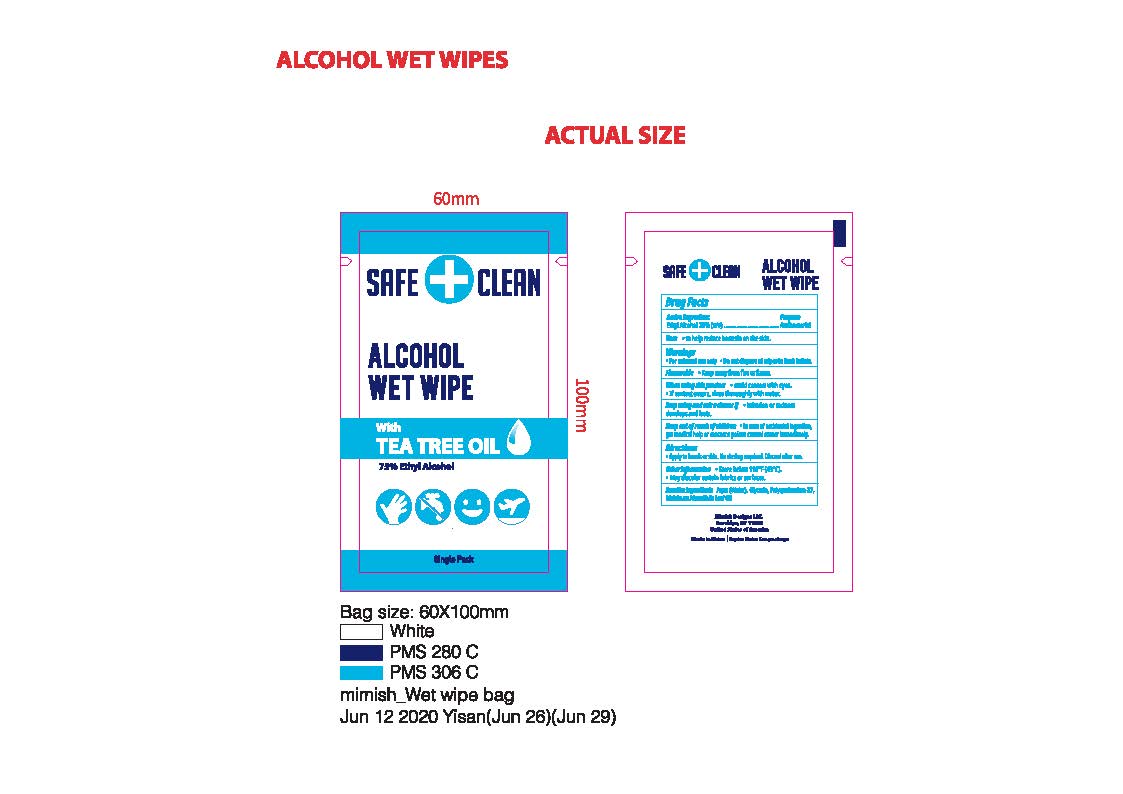 DRUG LABEL: Safe Clean Wet wipe
NDC: 79312-102 | Form: SWAB
Manufacturer: Mimish Designs, LLC
Category: otc | Type: HUMAN OTC DRUG LABEL
Date: 20200630

ACTIVE INGREDIENTS: ALCOHOL 0.75 mL/1 1
INACTIVE INGREDIENTS: MELALEUCA ALTERNIFOLIA LEAF; GLYCERIN; POLYQUATERNIUM 37 (200 MPA.S); WATER

Safe+Clean Alcohol Wet Wipe

Active Ingredient

Ethyl Alcohol 75%

Purpose

Antibacterial

Uses

To help reduce bacteria on the skin.

Warnings

For External Use only. Do not dispose of wipes in flush toilets. Flammable. Keep away from heat or flame.

When using this product

Avoid contact with eyes. If contact occurs, rinse thoroughly with water.

Stop use and ask a doctor.

If irritation or redness develops and last.

Keep out of reach of children.

In case of accidental ingestion, get medical help or contact a Poison Control Center immediately.

Directions

Apply to hands or skin. No rinsing require/ Discard after use.

Other Information

Store below 110F (43C)

May discolor certain fabrics or surfaces.

Inactive Ingredients

Aqua (Water), Glycerin, Polyquaternium-37, Melaleuca Alternifolia Leaf Oil.